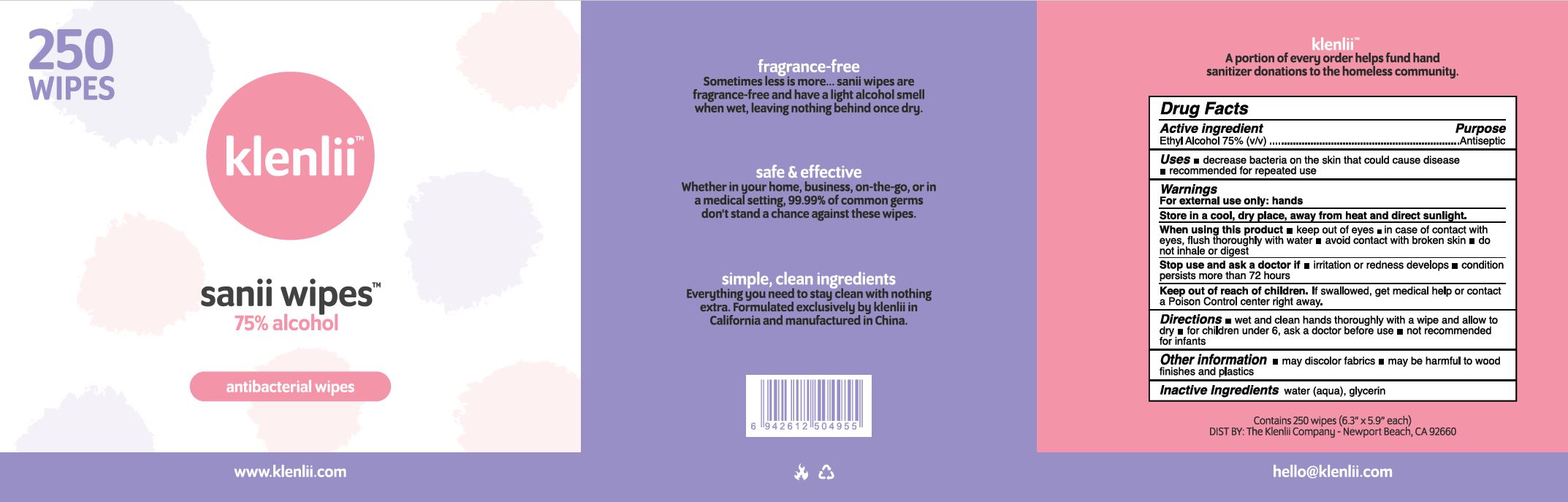 DRUG LABEL: KLENLII SANII WIPES
NDC: 78016-105 | Form: SOLUTION
Manufacturer: Klenlii Company
Category: otc | Type: HUMAN OTC DRUG LABEL
Date: 20240509

ACTIVE INGREDIENTS: ALCOHOL 7.5 mL/1 1
INACTIVE INGREDIENTS: WATER; GLYCERIN

KLENLII SANII WIPES (75% ETHYL ALCOHOL) (78016-105)

ACTIVE INGREDIENT

ETHYL ALCOHOL 75%

PURPOSE

ANTISEPTIC

USES

- DECREASE BACTERIA ON THE SKIN THAT COULD CAUSE DISEASE
- RECOMMENDED FOR REPEATED USE

WARNINGS

FOR EXTERNAL USE ONLY: HANDS

Store in a cool, dry place, away from heat and direct sunlight.

When using this product

- keep out of eyes
- in case of contact with eyes, flush thoroughly with water
- avoid contact with broken skin
- do not inhale or digest

Stop use and ask a doctor if

- irritation or redness develops
- condition persists more than 72 hours

KEEP OUT OF REACH OF CHILDREN. IF SWALLOWED, GET MEDICAL HELP OR CONTACT A POISON CONTROL CENTER RIGHT AWAY.

DIRECTIONS

- wet and clean hands thoroughly with a wipe and allow to dry
- for children under 6, ask a doctor before use
- not recommended for infants

OTHER INFORMATION

- may discolor fabrics
- may be harmful to wood finishes and plastics

INACTIVE INGREDIENTS

water (aqua), glycerin